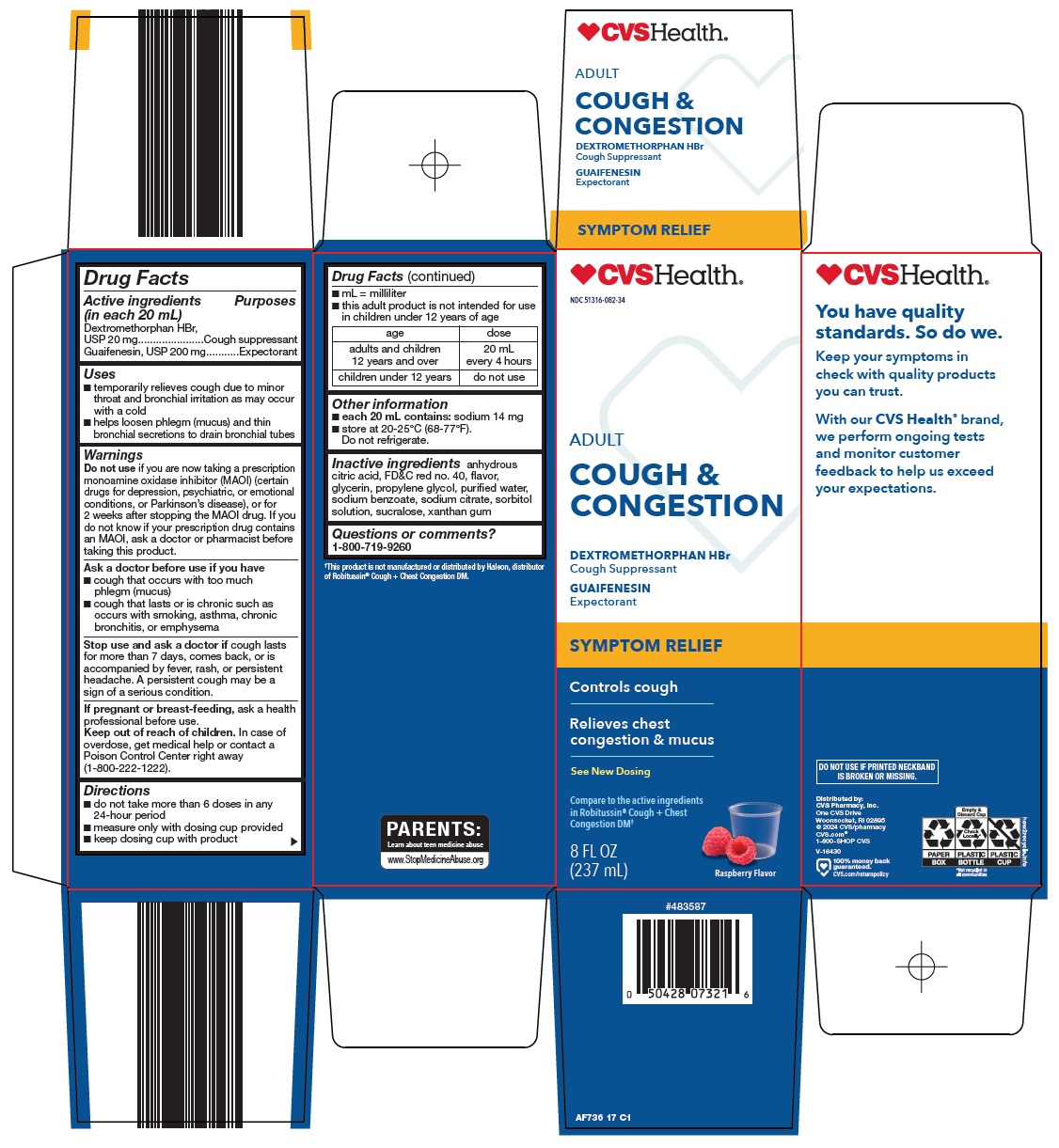 DRUG LABEL: COUGH AND CHEST CONGESTION
NDC: 51316-082 | Form: SOLUTION
Manufacturer: CVS WOONSOCKET PRESCRIPTION CENTER, INCORPORATED
Category: otc | Type: HUMAN OTC DRUG LABEL
Date: 20260217

ACTIVE INGREDIENTS: DEXTROMETHORPHAN HYDROBROMIDE 20 mg/20 mL; GUAIFENESIN 200 mg/20 mL
INACTIVE INGREDIENTS: ANHYDROUS CITRIC ACID; FD&C RED NO. 40; GLYCERIN; PROPYLENE GLYCOL; WATER; SODIUM BENZOATE; SODIUM CITRATE, UNSPECIFIED FORM; SORBITOL SOLUTION; SUCRALOSE; XANTHAN GUM

CVS Pharmacy, Inc. Cough & Congestion Drug Facts

Active ingredients (in each 20 mL)

Dextromethorphan HBr, USP 20 mg

Guaifenesin, USP 200 mg

Purposes

Cough suppressant

Expectorant

Uses

- temporarily relieves cough due to minor throat and bronchial irritation as may occur with a cold
- helps loosen phlegm (mucus) and thin bronchial secretions to drain bronchial tubes

Warnings

Do not use

if you are now taking a prescription monoamine oxidase inhibitor (MAOI) (certain drugs for depression, psychiatric, or emotional conditions, or Parkinson’s disease), or for 2 weeks after stopping the MAOI drug. If you do not know if your prescription drug contains an MAOI, ask a doctor or pharmacist before taking this product.

Ask a doctor before use if you have

- cough that occurs with too much phlegm (mucus)
- cough that lasts or is chronic such as occurs with smoking, asthma, chronic bronchitis, or emphysema

Stop use and ask a doctor if

cough lasts for more than 7 days, comes back, or is accompanied by fever, rash, or persistent headache. A persistent cough may be a sign of a serious condition.

If pregnant or breast-feeding,

ask a health professional before use.

Keep out of reach of children.

In case of overdose, get medical help or contact a Poison Control Center right away (1-800-222-1222).

Directions

- do not take more than 6 doses in any 24-hour period
- measure only with dosing cup provided
- keep dosing cup with product
- mL = milliliter
- this adult product is not intended for use in children under 12 years of age

age | dose
adults and children 12 years and over | 20 mL every 4 hours
children under 12 years | do not use

Other information

- each 20 mL contains: sodium 14 mg
- store at 20-25°C (68-77°F). Do not refrigerate.

Inactive ingredients

anhydrous citric acid, FD&C red no. 40, flavor, glycerin, propylene glycol, purified water, sodium benzoate, sodium citrate, sorbitol solution, sucralose, xanthan gum

Questions or comments?

1-800-719-9260

Package/Label Principal Display Panel

CVS Health®

ADULT

COUGH & CONGESTION

DEXTROMETHORPHAN HBr

Cough Suppressant

GUAIFENESIN

Expectorant

SYMPTOM RELIEF

Controls cough

Relieves chest congestion & mucus

See New Dosing

Compare to the active ingredients in Robitussin® Cough + Chest Congestion DM

8 FL OZ (237 mL)

Raspberry Flavor